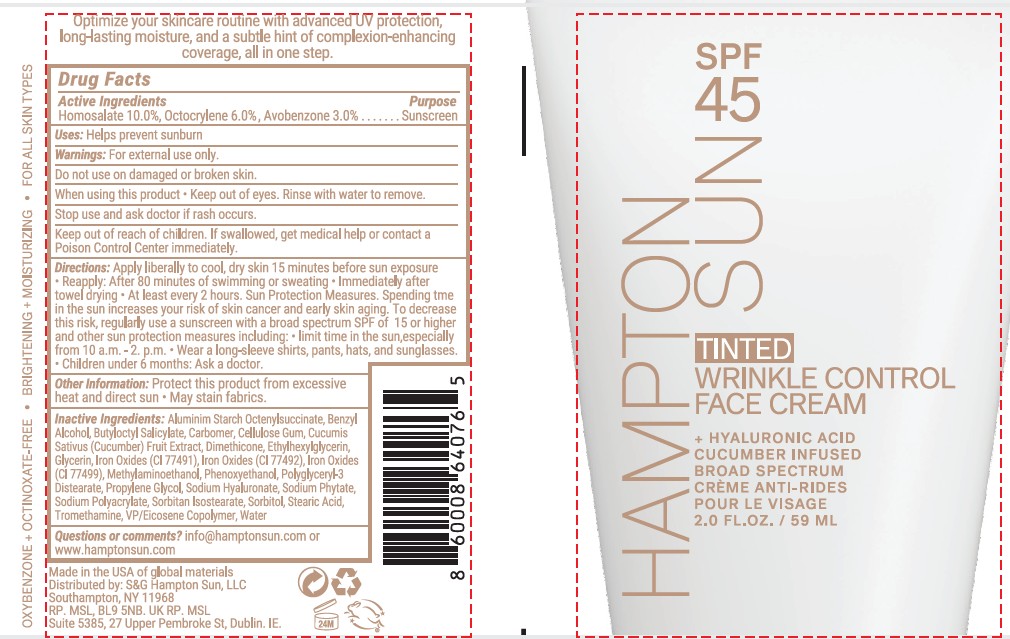 DRUG LABEL: Hampton Sun SPF 45 Tinted Face
NDC: 87170-009 | Form: CREAM
Manufacturer: S&C Hampton Sun LLC
Category: otc | Type: HUMAN OTC DRUG LABEL
Date: 20260128

ACTIVE INGREDIENTS: HOMOSALATE 10 g/100 mL; OCTOCRYLENE 6 g/100 mL; AVOBENZONE 3 g/100 mL
INACTIVE INGREDIENTS: ALUMINUM STARCH OCTENYLSUCCINATE; BENZYL ALCOHOL; BUTYLOCTYL SALICYLATE; CARBOMER; CELLULOSE GUM; CUCUMIS SATIVUS (CUCUMBER) FRUIT; DIMETHICONE; ETHYLHEXYLGLYCERIN; BROWN IRON OXIDE; PHENOXYETHANOL; POLYGLYCERYL-3 DISTEARATE; PROPYLENE GLYCOL; SODIUM HYALURONATE; SODIUM PHYTATE; SODIUM POLYACRYLATE (8000 MW); SORBITAN ISOSTEARATE; SORBITOL; STEARIC ACID; TROMETHAMINE; VINYLPYRROLIDONE/EICOSENE COPOLYMER; WATER

Hampton Sun SFP 45 Tinted Face Cream (IS0460-HST)

Actove Ingredeints Purpose

Homosalate 10% Sunscreen

Octoclylene 6% Sunscreen

Avobenzone 3% Sunscreen

Uses

Uses ■ helps prevent sunburn

DOSAGE AND ADMINISTRATION

Directionsapply liberally to cool, dry skin
15 minutes before sun exposure • reapply:
• after 80 minutes of swimming or sweating
• immediately after towel drying • at least every 2
hours • Sun Protection Measures. Spending time
in the sun increases your risk of skin cancer and
early skin aging. To decrease this risk, regularly
use a sunscreen with a broad spectrum SPF of 15
or higher and other sun protection measures
including: • limit time in the sun,especially from
10 a.m. - 2. p.m. • wear a long-sleeve shirts,
pants, hats, and sunglasses. • children under 6
months: Ask a doctor.

Warnings

For external use only.
Flammable: Do not use white smoking or near heat or flame.
Do not useon damaged or broken skin.
When using this product■ keep out of eyes. Rinse eyes with water
to remove.
Stop use and ask a doctor ifrash occurs.

Keep out of reach of children.if swallowed, get medical
help or contact a Polson Control Center right away.

Inactive Ingredients

ALUMINUM STARCH OCTENYLSUCCINATE
BENZYL ALCOHOL
BUTYLOCTYL SALICYLATE
CARBOMER
CELLULOSE GUM
CUCUMIS SATIVUS (CUCUMBER) FRUIT
DIMETHICONE
ETHYLHEXYLGLYCERIN
IRON OXIDEs
PHENOXYETHANOL
POLYGLYCERYL-3 DISTEARATE
SODIUM HYALURONATE
SODIUM PHYTATE
SODIUM POLYACRYLATE
SORBITAN ISOSTEARATE
SORBITOL
STEARIC ACID
TROMETHAMINE
VP /EICOSENE COPOLYMER
Water